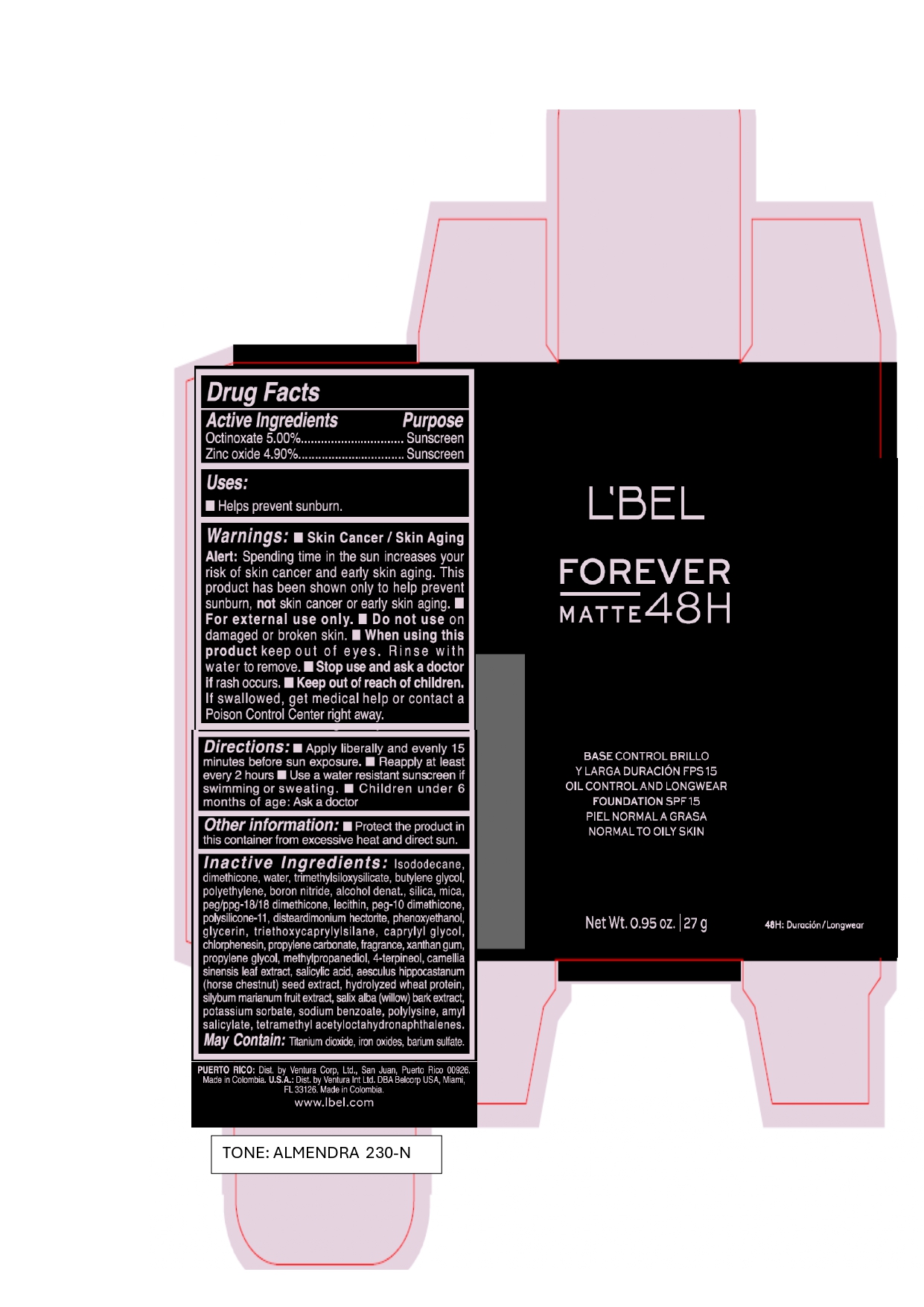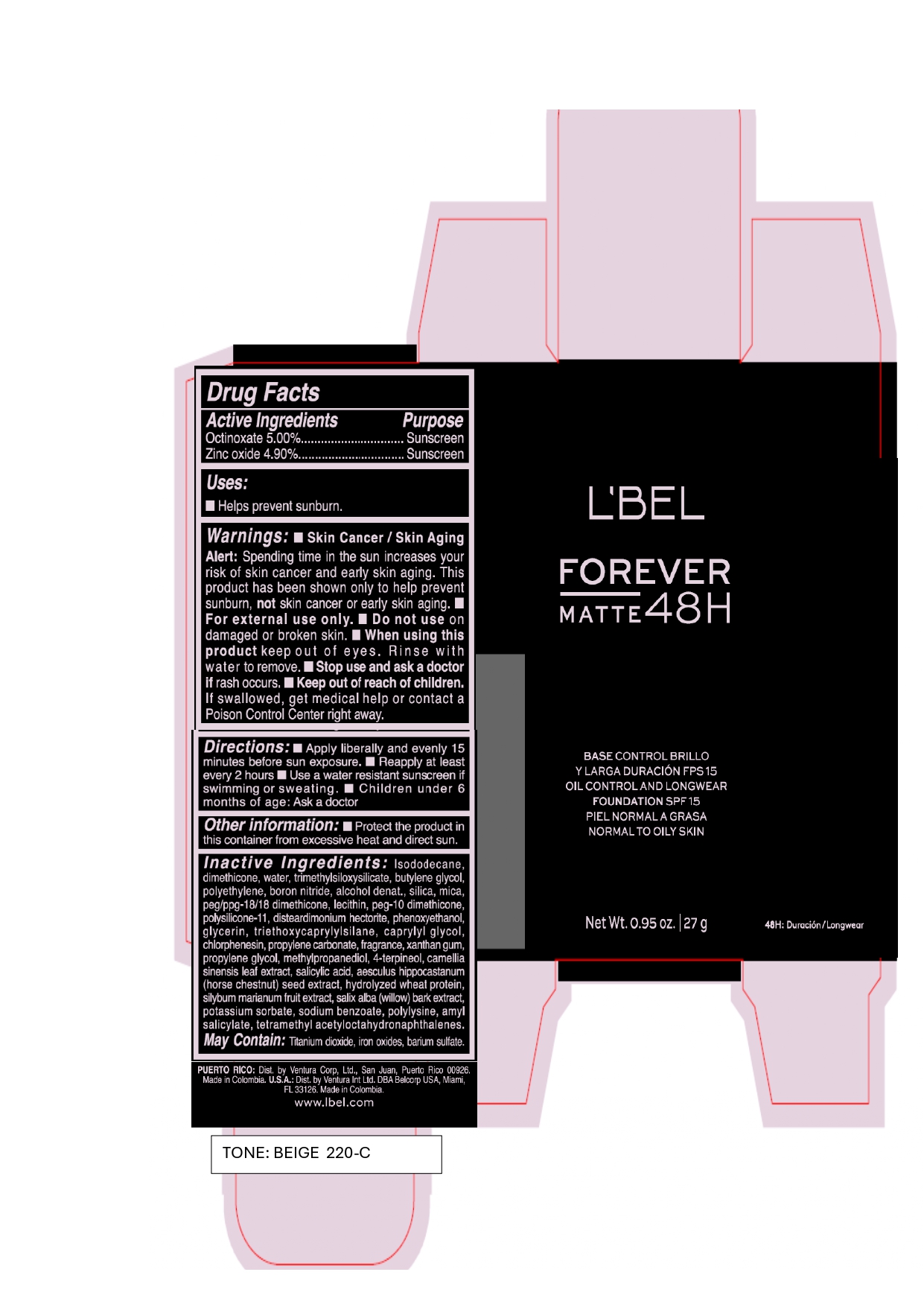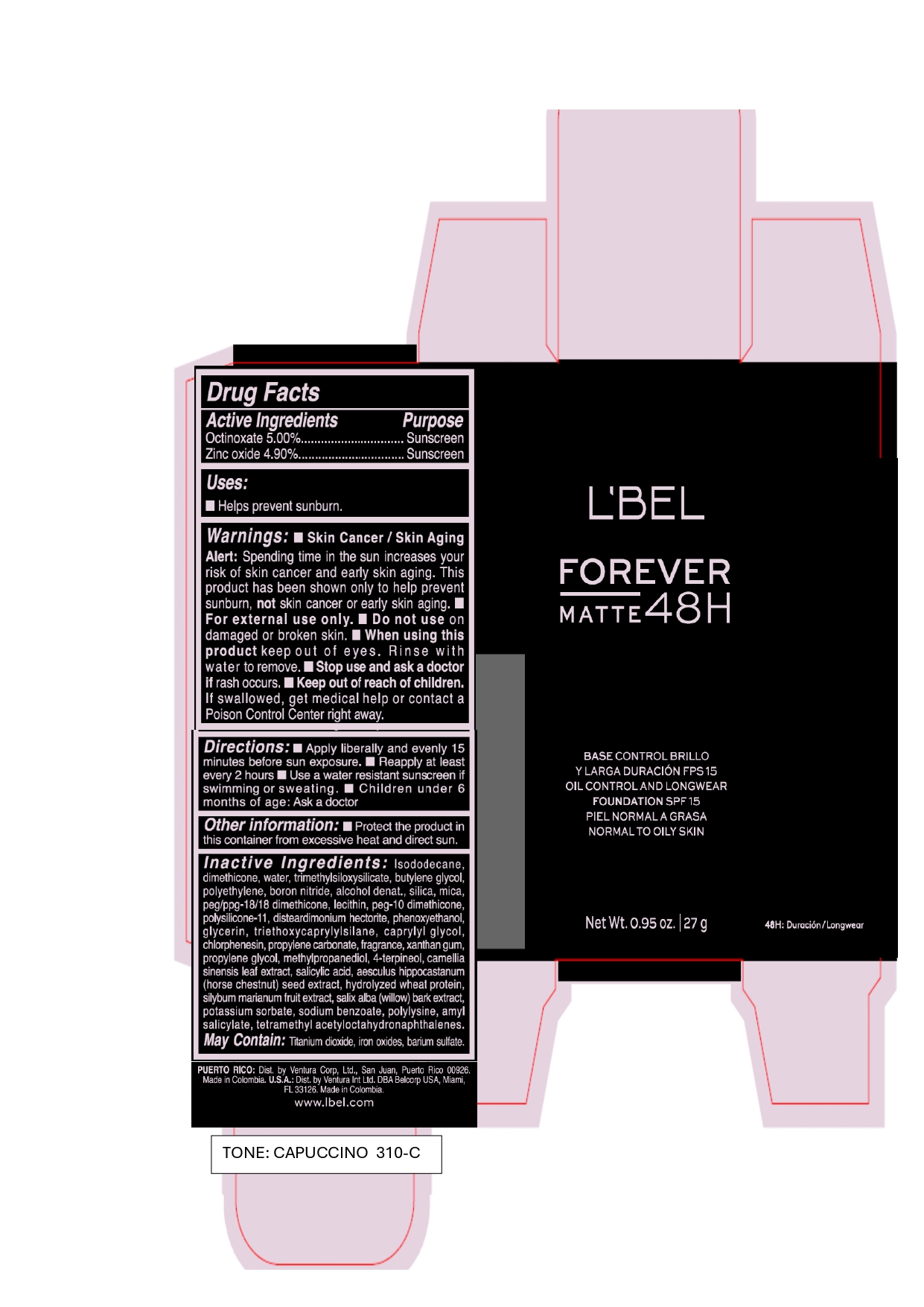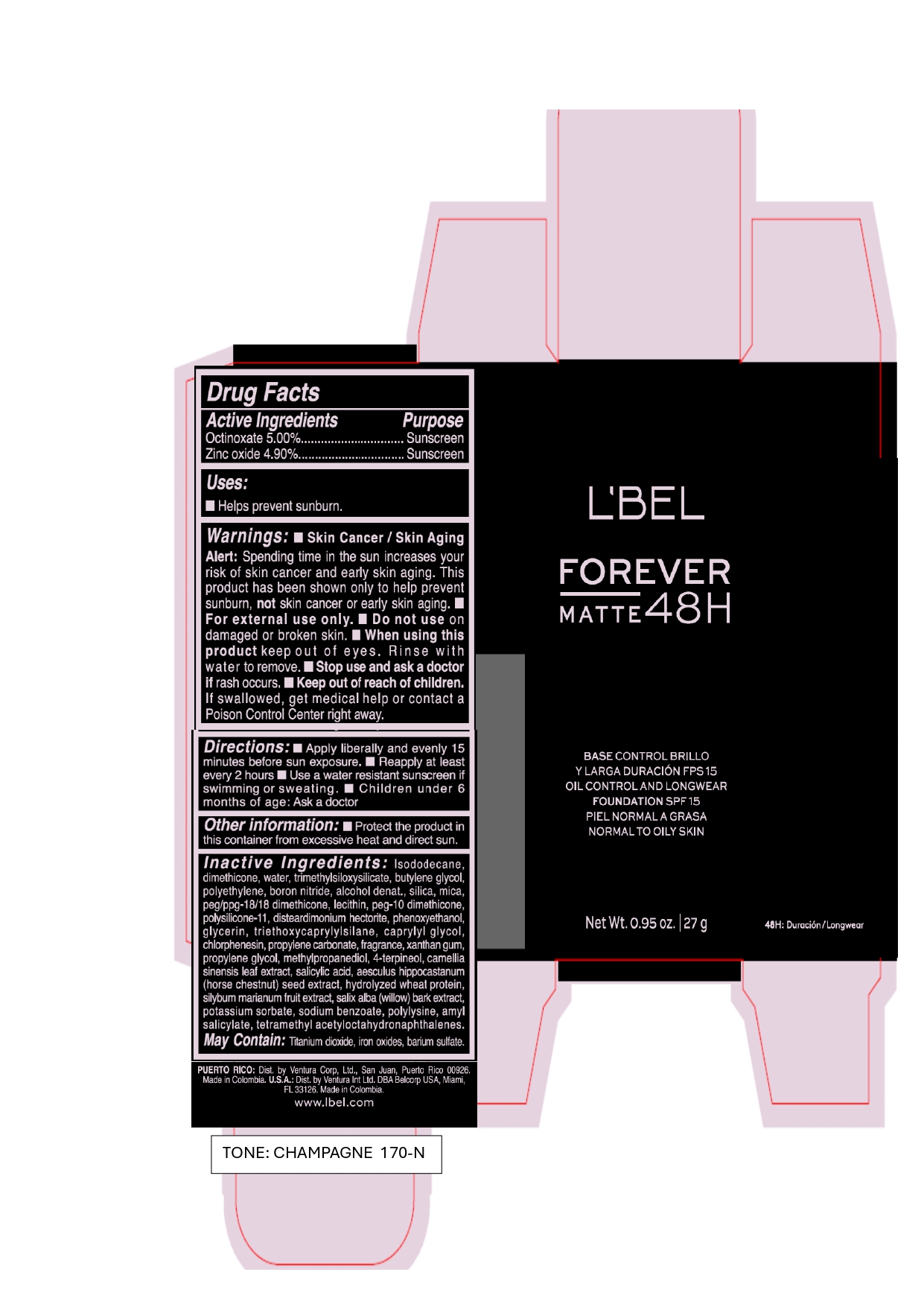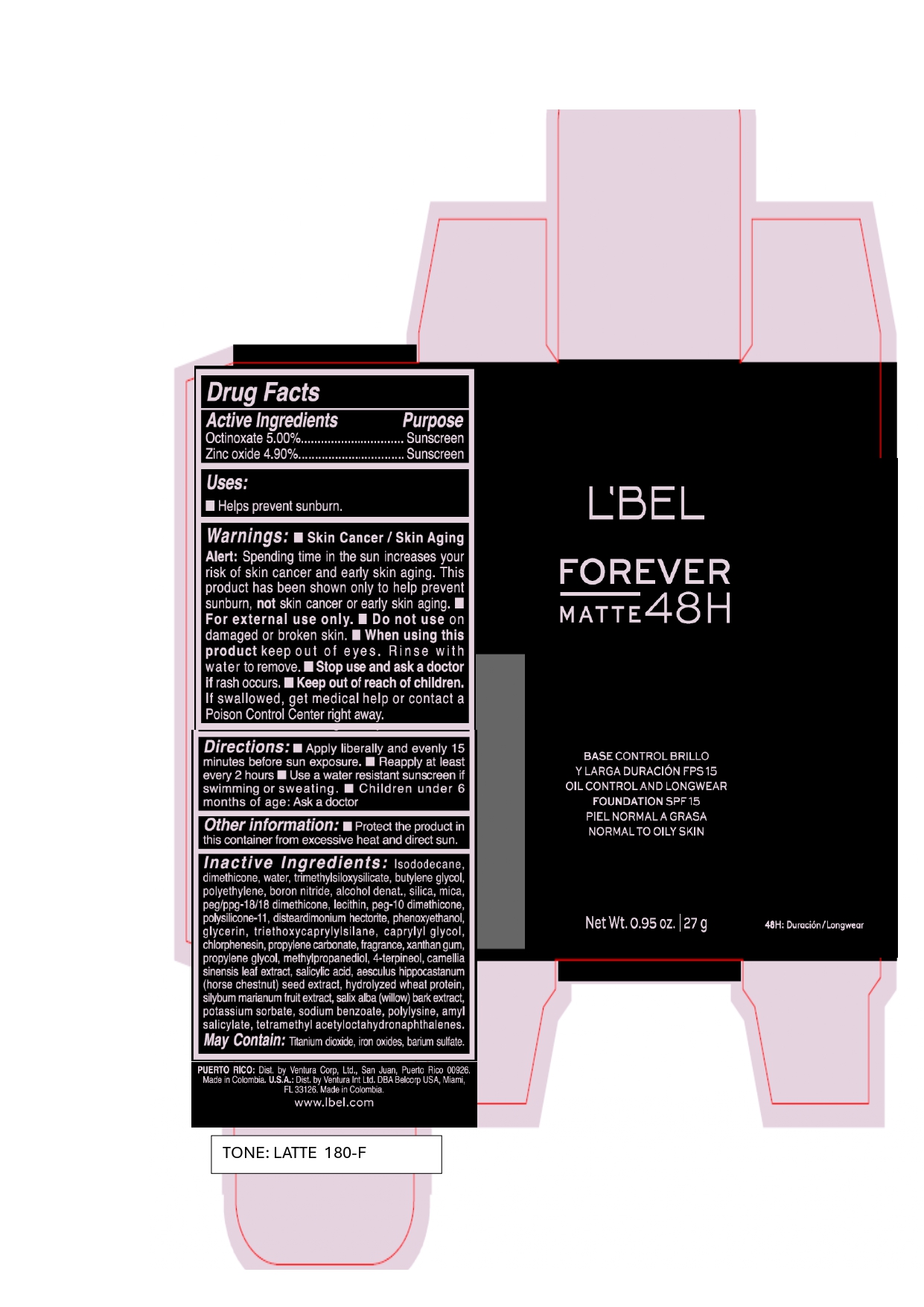 DRUG LABEL: LBEL FOREVER MATTE BASE CONTROL BRILLO Y LARGA DURACION 48H FPS 15 CONTROL AND LONGWEAR FOUNDATION 48H SPF 15 CHAMPAGNE 170-N
NDC: 14141-341 | Form: EMULSION
Manufacturer: BEL STAR S.A.
Category: otc | Type: HUMAN OTC DRUG LABEL
Date: 20240709

ACTIVE INGREDIENTS: OCTINOXATE 50 mg/1 g; ZINC OXIDE 49 mg/1 g
INACTIVE INGREDIENTS: SODIUM BENZOATE; METHYLPROPANEDIOL; SILICON DIOXIDE; CHLORPHENESIN; BUTYLENE GLYCOL; CAPRYLYL GLYCOL; BARIUM SULFATE; PROPYLENE CARBONATE; AMYL SALICYLATE; FERRIC OXIDE YELLOW; MICA; PEG/PPG-18/18 DIMETHICONE; LECITHIN, SUNFLOWER; DIMETHICONE/VINYL DIMETHICONE CROSSPOLYMER (SOFT PARTICLE); DISTEARDIMONIUM HECTORITE; PHENOXYETHANOL; TRIETHOXYCAPRYLYLSILANE; PROPYLENE GLYCOL; HIGH DENSITY POLYETHYLENE; ISODODECANE; XANTHAN GUM; POLY-L-LYSINE (30000-70000 MW); FERRIC OXIDE RED; ALCOHOL; SALICYLIC ACID; POTASSIUM SORBATE; DIMETHICONE; GLYCERIN; 4-TERPINEOL, (+)-; GREEN TEA LEAF; SALIX ALBA BARK; HORSE CHESTNUT; BORON NITRIDE; WATER; FERROSOFERRIC OXIDE; MILK THISTLE; TETRAMETHYL ACETYLOCTAHYDRONAPHTHALENES; TRIMETHYLSILOXYSILICATE (M/Q 0.6-0.8); HYDROLYZED WHEAT PROTEIN (ENZYMATIC, 3000 MW); TITANIUM DIOXIDE; PEG-10 DIMETHICONE (600 CST)

LBEL FOREVER MATTE BASE CONTROL BRILLO Y LARGA DURACION 48H FPS 15 OIL CONTROL AND LONGWEAR FOUNDATION 48H SPF 15

Active Ingredients

Octinoxate 5.00%

Zinc oxide 4.90%

Purpose

Sunscreen

Uses

- Helps prevent sunburn

Warnings

- Skin Cancer/Skin Aging Alert: Spending time in the sun increases your risk of skin cancer and early skin aging. This product has been shown only to help prevent sunburn, not skin cancer or early skin aging.
- For external use only.

Do not use

on damaged or broken skin.

When using this product

keep out of eyes. Rinse with water to remove.

Stop use and ask a doctor

if rash occurs.

Keep out of reach of children.

If swallowed, get medical help or contact a Poison Control Center right away.

Directions

- Apply liberally and evenly 15 minutes before sun exposure.
- Reapply at least every 2 hours.
- Use a water resistant sunscreen if swimming or sweating.
- Children under 6 months of age: Ask a doctor

Other information

- Protect the product in this container from excessive heat and direct sun.

Inactive Ingredients

Isododecane, dimethicone, water, trimethylsiloxysilicate, butylene glycol, polyethylene, boron nitride, alcohol denat., silica, mica, peg/ppg-18/18 dimethicone, lecithin, peg-10 dimethicone, polysilicone-11, disteardimonium hectorite, phenoxyethanol, glycerin, triethoxycaprylylsilane, caprylyl glycol, chlorphenesin, propylene carbonate, fragrance, xanthan gum, propylene glycol, methylpropanediol, 4-terpineol, camellia sinensis leaf extract, salicylic acid, aesculus hippocastanum (horse chestnut) seed extract, hydrolyzed wheat protein, silybum marianum fruit extract, ‎salix alba ‎(‎willow‎) ‎bark ‎extract, potassium sorbate, sodium benzoate, polylysine, amyl salicylate, tetramethyl acetyloctahydronaphthalenes.

May Contain :

Titanium dioxide, iron oxides, barium sulfate.

Company Information

PUERTO RICO: Dist. by Ventura Corp, Ltd., San Juan, Puerto Rico 00926

Made in Colombia. U.S.A.: Dist. by Ventura Int Ltd. DBA Belcorp USA, Miami, FL 33126. Made in Colombia.

www.lbel.com